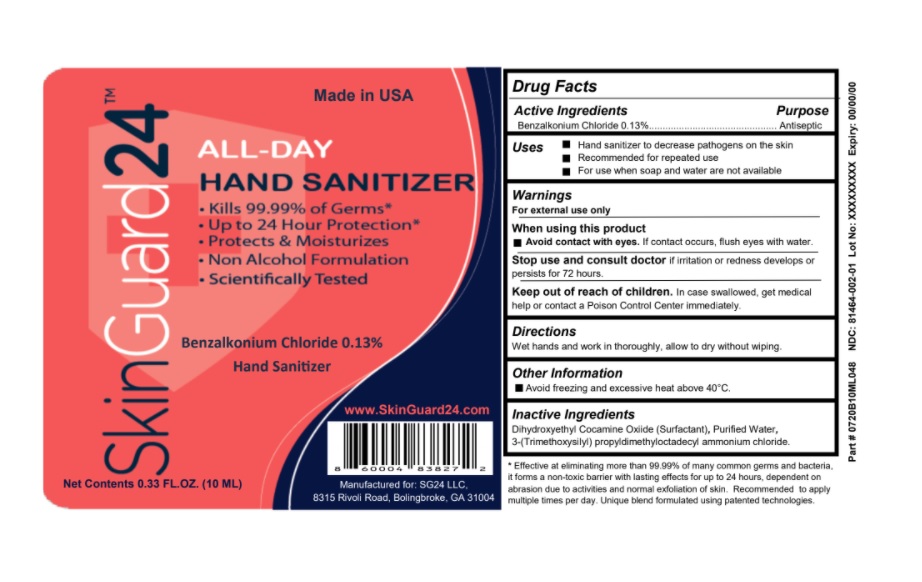 DRUG LABEL: SkinGuard24
NDC: 81464-002 | Form: LIQUID
Manufacturer: SG24, LLC
Category: otc | Type: HUMAN OTC DRUG LABEL
Date: 20231010

ACTIVE INGREDIENTS: BENZALKONIUM CHLORIDE 0.13 g/100 mL
INACTIVE INGREDIENTS: WATER; DIHYDROXYETHYL COCAMINE OXIDE; .GAMMA.-METHACRYLOXYPROPYLTRIMETHOXYSILANE

Active Ingredient

Benzalkonium Chloride 0.13%

Purpose

Antiseptic

Uses

Hand sanitizer to decrease pathogens on the skin
Recommended for repeated use
For use when soap and water are not available

Warnings

For external use only. Avoid contact with the eyes.

When using this product
Avoid contact with eyes. If contact occurs, flush eyes with water.

Stop use and consult doctorif irritation or redness develops or
persists for 72 hours.

Keep out of reach of children.

In case swallowed, get medical help or contact a Poison Control Center immediately.

Directions

Wet hands and work in thoroughly, allow to dry without wiping.

Other Information

Avoid freezing and excessive heat above 40°C.

Inactive Ingredients

Dihydroxyethyl Cocamine Oxiide (Surfactant), Purified Water, 3-(Trimethoxysilyl) propyldimethyloctadecyl ammonium chloride.